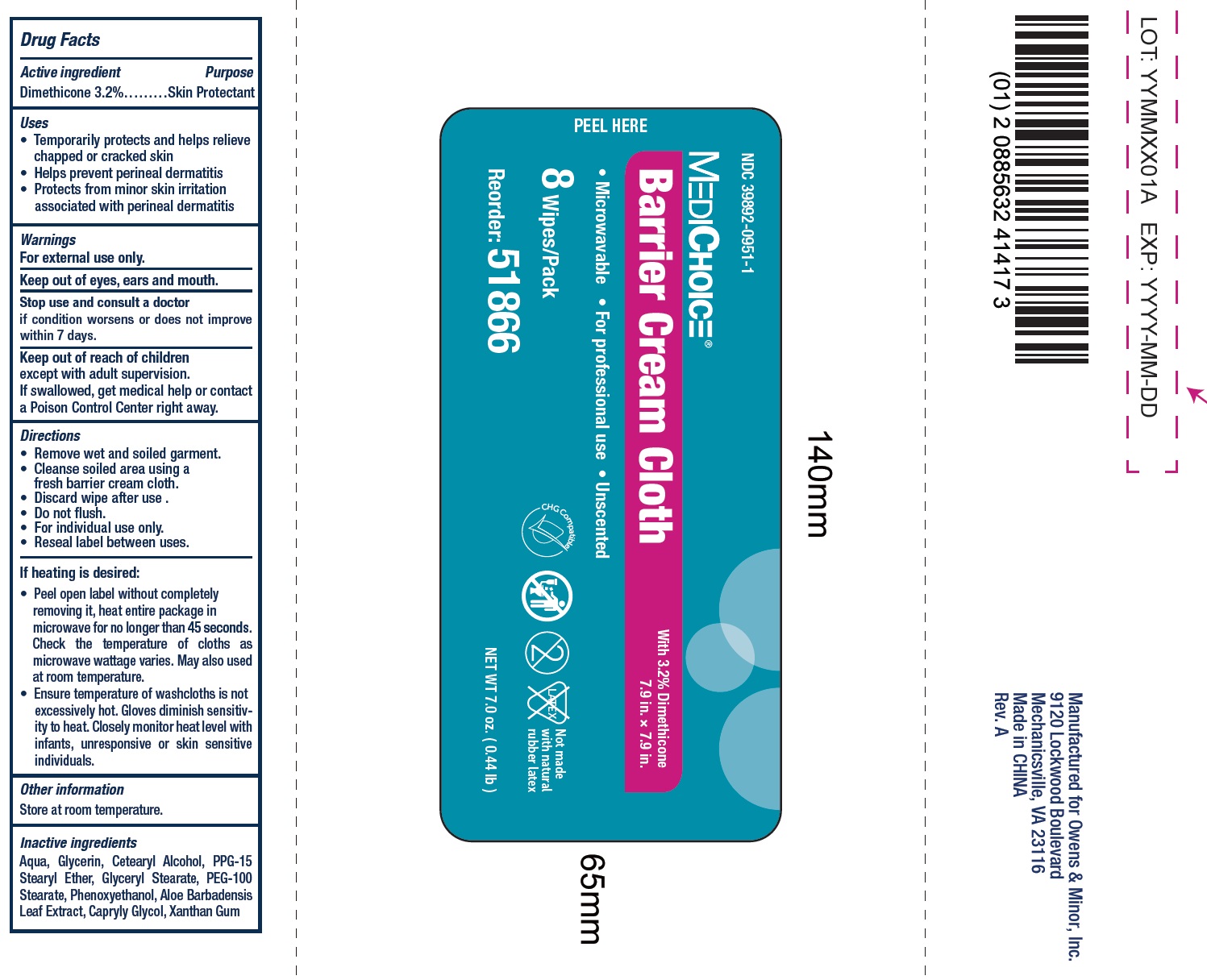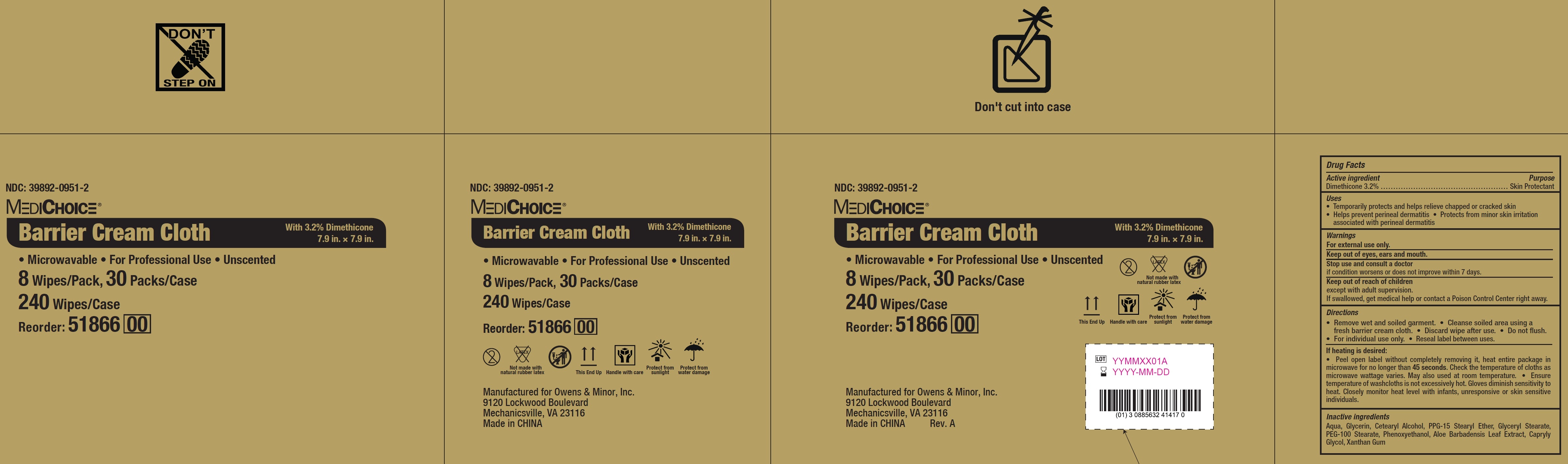 DRUG LABEL: MediChoice Barrier
NDC: 39892-0951 | Form: CLOTH
Manufacturer: O&M HALYARD, INC.
Category: otc | Type: HUMAN OTC DRUG LABEL
Date: 20251009

ACTIVE INGREDIENTS: DIMETHICONE 32 mg/1 g
INACTIVE INGREDIENTS: WATER; GLYCERIN; CETOSTEARYL ALCOHOL; PPG-15 STEARYL ETHER; GLYCERYL MONOSTEARATE; PEG-100 STEARATE; PHENOXYETHANOL; ALOE VERA LEAF; CAPRYLYL GLYCOL; XANTHAN GUM

MediChoice Barrier Cream

Active ingredient

Dimethicone 3.2%

Purpose

Skin Protectant

Uses

• Temporarily protects and helps relieve chapped or cracked skin
• Helps prevent perineal dermatitis • Protects from minor skin irritation associated with perineal dermatitis

Warnings

For external use only.
Keep out of eyes, ears and mouth.

Stop use and consult a doctor

if condition worsens or does not improve within 7 days.

Keep out of reach of children

except with adult supervision. If swallowed, get medical help or contact a Poison Control Center right away.

Directions

• Remove wet and soiled garment. • Cleanse soiled area using a fresh barrier cream cloth. • Discard wipe after use. • Do not flush. • For individual use only. • Reseal label between uses.

If heating is desired:

• Peel open label without completely removing it, heat entire package in microwave for no longer than 45 seconds. Check the temperature of cloths as microwave wattage varies. May also used at room temperature. • Ensure temperature of washcloths is not excessively hot. Gloves diminish sensitivity to heat. Closely monitor heat level with infants, unresponsive or skin sensitive individuals.

Inactive ingredients

Aqua, Glycerin, Cetearyl Alcohol, PPG-15 Stearyl Ether, Glyceryl Stearate, PEG-100 Stearate, Phenoxyethanol, Aloe Barbadensis Leaf Extract, Capryly Glycol, Xanthan Gum